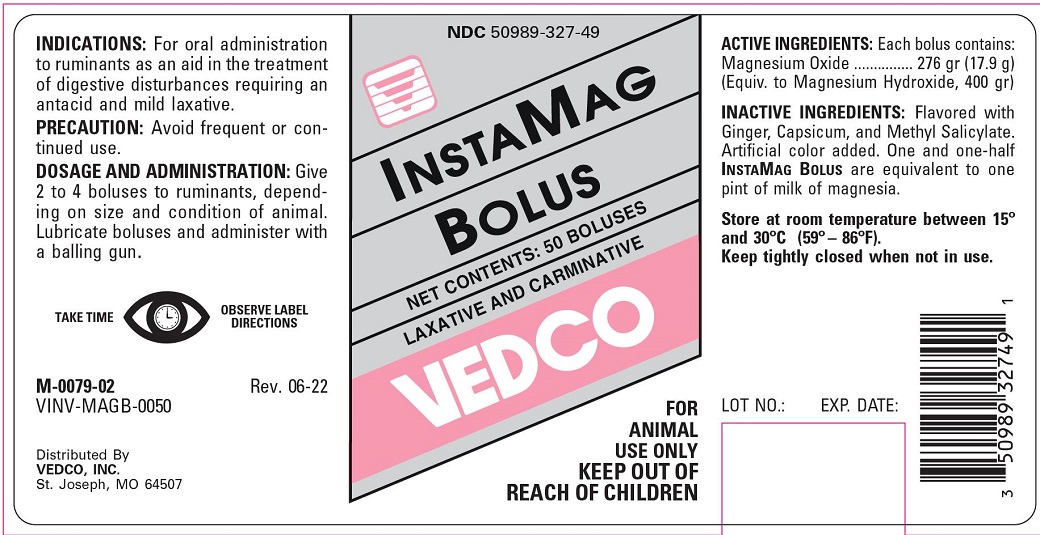 DRUG LABEL: INSTAMAG
NDC: 50989-327 | Form: TABLET
Manufacturer: Vedco, Inc.
Category: animal | Type: OTC ANIMAL DRUG LABEL
Date: 20221115

ACTIVE INGREDIENTS: MAGNESIUM OXIDE 276 g/1 1

INSTAMAG BOLUS

INDICATIONS AND USAGE

ANTIACID OR MILD LAXATIVE

FOR ANIMAL USE ONLY

KEEP OUT OF REACH OF CHILDREN

INDICATIONS

For oral administration as an aid in the treatment of digestive disturbances requiring an antacid or mild laxative in cattle.

PRECAUTION

Avoid frequent or continued use.

DOSAGE AND ADMINISTRATION

Give 2 to 4 boluses to ruminants, depending on size and condition of animal. Lubricate boluses and adminster with a balling gun.

COMPOSITION

Each bolus contains:

Magnesium Oxide ...... 276 grs. (17.9 g)
(Equivalent to Magnesium Hydroxide, 400 grs.)
Flavored with Ginger, Capsicum, and Methyl Salicylate. Artificial color added. One and one-half InstaMag Bolus are equivalent to one pint of milk of magnesia.

STORAGE AND HANDLING

Store at room temperature between 15° and 30°C (59°-86°F).

Keep tightly closed when not in use.

TAKE TIME TO OBSERVE LABEL DIRECTIONS